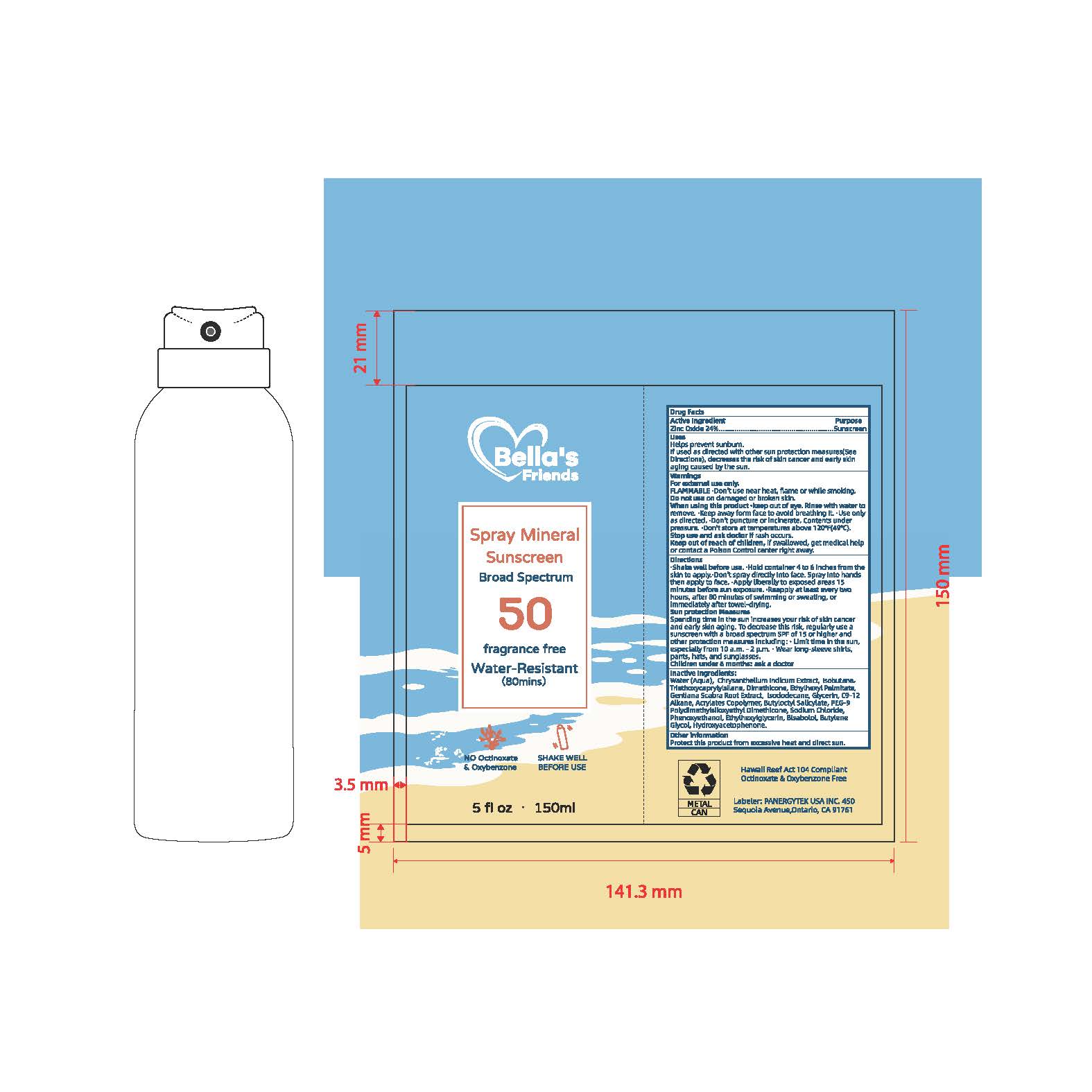 DRUG LABEL: Bella s Friends SPF50 Sunscreen
NDC: 85950-005 | Form: SPRAY
Manufacturer: PANERGYTEK USA INC
Category: otc | Type: HUMAN OTC DRUG LABEL
Date: 20260120

ACTIVE INGREDIENTS: ZINC OXIDE 24 g/100 mL
INACTIVE INGREDIENTS: HYDROXYACETOPHENONE; BUTYL ACRYLATE/METHYL METHACRYLATE/METHACRYLIC ACID COPOLYMER (18000 MW); DIMETHICONE; C9-12 ALKANE; ISODODECANE; ETHYLHEXYLGLYCERIN; WATER; PEG-9 POLYDIMETHYLSILOXYETHYL DIMETHICONE; ISOBUTANE; TRIETHOXYCAPRYLYLSILANE; BISABOLOL; ETHYLHEXYL PALMITATE; GLYCERIN; BUTYLOCTYL SALICYLATE; CHRYSANTHELLUM INDICUM TOP; GENTIANA SCABRA ROOT; SODIUM CHLORIDE; PHENOXYETHANOL

Active Ingredient
Zinc Oxide 24%.......
..
PurposeSunscreen

Uses
Helps prevent sunburn.If used as directed with other sun protection measures(SeeDirections), decresses the risk of skin cancer and early skin aging caused by the sun.

Keep out of reach of children, if swallowed, get medical help or contact a Poison Control center right away.

WARNINGS

WarningsFor external use only. FLAMMABLE.Don't use near heat, flame or while smoking.Do not use on damaged or broken skin.When using this product .keep out of eye. Rinse with water to remove. Keep away form face to avoid breathing it. .Use only as directed. .Don't puncture or incinerate. Contents underpressure..Don't store at temperatures above 120F(49C).

INDICATIONS AND USAGE

Sun protection Measures Spending time in the sun increases your risk of skin cancer and early skin aging. To decrease this risk, regularly use a sunscreen with a broad spectrum SPF of 15 or higher and other protection measures including:. Limit time in the sun,especially from 10 a.m. - 2 p.m..Wear long-sleeve shirts,pants, hats, and sunglasses.

DOSAGE AND ADMINISTRATION

hake well before use. .Hold container 4 to 6 inches from the skin to apply.-Don't spray directly into face. Spray into hands then apply to face. .Apply liberally to exposed areas 15 minutes before sun exposure. Reapply at least every two hours, after 80 minutes of swimming or sweating, or immediately after towel-drying

INACTIVE INGREDIENT

Inactive Ingredients: Water (Aqua), Chrysanthellum Indicum Extract, Isobutane,Triethoxycaprylylsilane, Dimethicone, Ethylhexyl Palmitate,Gentiana Scabra Root Extract, Isododecane, Glycerin, C9-12 Alkane, Acrylates Copolymer, Butyloctyl Salicylate, PEG-9 Polydimethylsiloxyethyl Dimethicone, Sodium Chloride,Phenoxyethanol, Ethylhexylglycerin, Bisabolol, ButyleneGlycol, Hydroxyacetophenone.